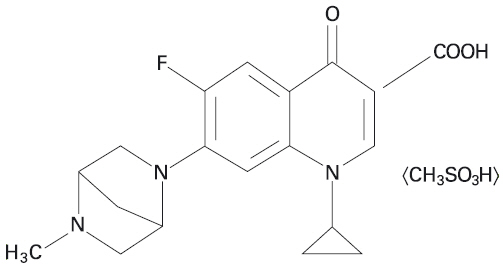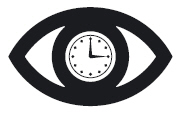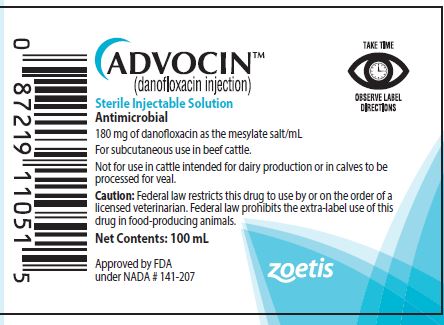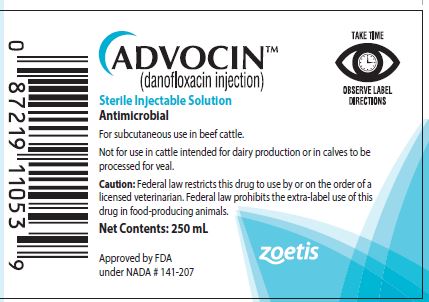 DRUG LABEL: Advocin
NDC: 54771-9847 | Form: INJECTION, SOLUTION
Manufacturer: Zoetis Inc.
Category: animal | Type: PRESCRIPTION ANIMAL DRUG LABEL
Date: 20210303

ACTIVE INGREDIENTS: DANOFLOXACIN MESYLATE 180 mg/1 mL
INACTIVE INGREDIENTS: PYRROLIDONE 200 mg/1 mL; POVIDONE 50 mg/1 mL; MAGNESIUM OXIDE 20.3 mg/1 mL; PHENOL 2.5 mg/1 mL; MONOTHIOGLYCEROL 5 mg/1 mL; WATER

ADVOCIN™
(danofloxacin injection)

Sterile Injectable Solution

Antimicrobial

180 mg of danofloxacin as the mesylate salt/mL

For subcutaneous use in beef cattle.

Not for use in cattle intended for dairy production or in calves to be processed for veal.

CAUTION

Federal law restricts this drug to use by or on the order of a licensed veterinarian. Federal law prohibits the extra-label use of this drug in food-producing animals.

DESCRIPTION

ADVOCIN is a sterile injectable solution containing danofloxacin mesylate, a synthetic fluoroquinolone antimicrobial agent. Danofloxacin mesylate is the non-proprietary designation for (1S)-1cyclopropyl-6-fluoro-1,4-dihydro-7-(5-methyl-2,5-diazabicyclo [2.2.1]hept-2-yl)-4-oxo-3-quinolone carboxylic acid monomethanesulfonate. The empirical formula is C19H20FN3O3 • CH3SO3H and the molecular weight is 453.49.

Figure 1. The chemical structure of danofloxacin mesylate.

Each mL contains 180 mg of danofloxacin as the mesylate salt, 200 mg 2-pyrrolidone, 50 mg polyvinyl pyrrolidone, 20.3 mg heavy magnesium oxide, 2.5 mg phenol, 5 mg monothioglycerol, hydrochloric acid or sodium hydroxide as needed to adjust pH, nitrogen headspace and water for injection, q.s.

INDICATIONS

For the treatment of bovine respiratory disease (BRD) associated with Mannheimia haemolytica and Pasteurella multocida in beef cattle and for the control of BRD in beef cattle at high risk of developing BRD associated with Mannheimia haemolytica and Pasteurella multocida.

DOSAGE AND ADMINISTRATION

Care should be taken to dose accurately. Administered dose volume should not exceed 15 mL per injection site.

Single-Dose Therapy (BRD Treatment and Control in Cattle at High Risk):

Administer subcutaneously at 8 mg/kg of body weight (2 mL/100 lb) as a one-time injection.

Multi-Day Therapy (BRD Treatment):

Administer subcutaneously at 6 mg/kg of body weight (1.5 mL/100 lb) with this treatment repeated once approximately 48 hours following the first injection.

ADVOCIN Dosage and Treatment Schedule
 | Dose Volume (mL)
Cattle Weight (lb) | 6 mg/kg, given twice, 48 hours apart (treatment) | 8 mg/kg given once (treatment and control in cattle at high risk)
50 | 0.75 | 1
100 | 1.5 | 2
150 | 2.25 | 3
200 | 3 | 4
250 | 3.75 | 5
300 | 4.5 | 6
400 | 6 | 8
500 | 7.5 | 10
600 | 9 | 12
700 | 10.5 | 14
800 | 12 | 16 [Administered dose volume should not exceed 15 mL per injection site.]
900 | 13.5 | 18
1000 | 15 | 20

* Administered dose volume should not exceed 15 mL per injection site.

Clinical field studies indicate that ADVOCIN (danofloxacin injection) Sterile Injectable Solution is effective for the control of respiratory disease in beef cattle at high risk of developing BRD. Cattle at high risk of developing BRD typically experience one or more of the following risk factors:

• Commingling from multiple sale barns/sources

• Extended transport times and shrink

• Exposure to wet or cold weather conditions or wide temperature swings

• Stressful arrival processing procedures (such as castration, dehorning, or branding)

• Recent weaning or poor vaccination history

RESIDUE WARNINGS

Animals intended for human consumption must not be slaughtered within 4 days from the last treatment. Do not use in cattle intended for dairy production. A withdrawal period has not been established for this product in preruminating calves. Do not use in calves to be processed for veal.

HUMAN WARNINGS

For use in animals only. Keep out of reach of children. Avoid contact with eyes. In case of contact, immediately flush eyes with copious amounts of water for 15 minutes. In case of dermal contact, wash skin with soap and water. Consult a physician if irritation persists following ocular or dermal exposures. Individuals with a history of hypersensitivity to quinolones should avoid this product. In humans, there is a risk of user photosensitization within a few hours after excessive exposure to quinolones. If excessive accidental exposure occurs, avoid direct sunlight. To report adverse reactions or to obtain a copy of the Safety Data Sheet (SDS), call 1-888-963-8471.

PRECAUTIONS

The effects of danofloxacin on bovine reproductive performance, pregnancy, and lactation have not been determined.

Subcutaneous injection can cause a transient local tissue reaction that may result in trim loss of edible tissue at slaughter.

Quinolone-class drugs should be used with caution in animals with known or suspected central nervous system (CNS) disorders. In such animals, quinolones have, in rare instances, been associated with CNS stimulation, which may lead to convulsive seizures.

Quinolone-class drugs have been shown to produce erosions of cartilage of weight-bearing joints and other signs of arthropathy in immature, rapidly growing animals of various species. Refer to Animal Safety for information specific to danofloxacin.

ADVERSE REACTIONS

A hypersensitivity reaction was noted in 2 healthy calves treated with ADVOCIN in a laboratory study. In one location of a multi-site field trial, one out of the 41 calves treated with 6 mg/kg q 48 hours showed lameness on Day 6 only. In this same field trial location one of 38 calves treated with 8 mg/kg once became lame 4 days after treatment and remained lame on the last day of the study (Day 10). Another calf in the same treatment group developed lameness on the last day of the study.

CLINICAL PHARMACOLOGY

(a) Pharmacokinetics

Danofloxacin distributes extensively throughout the body, as evidenced by a steady state volume of distribution (VDss) in cattle exceeding 1 L/kg. Danofloxacin concentrations in the lung homogenates markedly exceed those observed in plasma, further suggesting extensive distribution to the indicated site of infection. Danofloxacin is rapidly eliminated from the body (apparent terminal elimination T. ranging from 3–6 hours), and negligible accumulation was observed when animals were dosed twice, 48 hours apart.

Danofloxacin is rapidly absorbed and is highly bioavailable when administered as a subcutaneous injection in the neck. Linear pharmacokinetics has been demonstrated when danofloxacin is administered to cattle by subcutaneous injection at doses between 1.25 to 10 mg/kg.

No statistically significant gender difference was observed in peak or total systemic exposure following a single subcutaneous administration of danofloxacin to heifers and steers at a dose of 6 mg/kg body weight (Table 1).

Table 1. Danofloxacin pharmacokinetic values in male and female cattle (n=6/group) after a single subcutaneous injection into the lateral neck region at a dose of 6 mg danofloxacin/kg body weight
 |  | Steers | Heifers
 |  | Mean | %CV [Coefficient of variation %] | Mean | %CV
aAUC0-24 | µg × hr/mL | 9.4 | 10 | 8.8 | 9
bF% |  | 92 | 5 | 87 | 3
aCmax | µg/mL | 1.25 | 16 | 1.27 | 13
a,cTmax | hr | 3.2 | 42 | 1.7 | 31
dCL | L/hr | 0.54 | 12 | 0.62 | 9
dVDss | L/kg | 2.7 | 7 | 2.6 | 4
aT½ | hr | 4.8 | 18 | 4.2 | 7

a AUC0-24 = area under the plasma concentration versus time curve from hr zero to hr 24 postdose. Cmax = maximum observed concentration. Tmax = time to Cmax.
b Bioavailability (F%) = extent of drug absorption following subcutaneous administration. Within subject F values were determined as the ratio of AUC0-inf values estimated following a 6 mg/kg dose administered by either a subcutaneous or intravenous injection.
c Statistically significant differences in Tmax were detected between genders. Given the similarity in Cmax values, these differences are not expected to have any clinical relevance.
d Clearance (CL) and Volume of distribution at steady state (VDss) were determined from data obtained after intravenous administration of a 6 mg/kg dose.
e Coefficient of variation %

(b) Microbiology

Danofloxacin exerts its activity by inhibiting the bacterial DNA gyrase enzyme, thereby blocking DNA replication. Inhibition of DNA gyrase is lethal to bacteria and danofloxacin has been shown to be rapidly bactericidal. Danofloxacin is active against gram-negative and gram-positive bacteria.

The Minimum Inhibitory Concentrations (MIC) of danofloxacin for pathogens isolated in natural infections from various clinical studies in North America, 1996–1997, were determined using the standardized microdilution technique (Sensititre/Alamar, Accumed International), and are shown in Table 2

Table 2. Danofloxacin minimum inhibitory concentration (MIC) values* of indicated pathogens isolated from 1996-1997 pivotal BRD treatment field studies in the U.S.
Indicated Pathogen | Number of Isolates | MIC50**; (μg/ mL) | MIC90**; (μg/ mL) | MIC Range (μg/ mL)
Mannheimia haemolytica | 106 | 0.06 | 0.06 | ≤0.015 to 0.12
Pasteurella multocida | 94 | ≤0.015 | 0.06 | ≤0.015 to 0.12

* The correlation between in vitro susceptibility data and clinical effectiveness is unknown.
** The lowest MIC to encompass 50% and 90% of the most susceptible isolates, respectively.
Table 3. Danofloxacin minimum inhibitory concentration (MIC) values* of indicated pathogens isolated from 2013 pivotal field studies in the U.S. and Canada for the control of BRD in cattle at high risk of developing BRD.
Indicated Pathogen | Number of Isolates | MIC50**; (μg/ mL) | MIC90**; (μg/ mL) | MIC Range (μg/ mL)
Mannheimia haemolytica | 507 | 0.03 | 0.06 | ≤0.008 to >8
Pasteurella multocida | 324 | ≤0.008 | 0.12 | ≤0.008 to 1.0

*The correlation between in vitro susceptibility data and clinical effectiveness is unknown.
**The lowest MIC to encompass 50% and 90% of the most susceptible isolates, respectively.

EFFECTIVENESS

The effectiveness of 8 mg/kg administered once and the 6 mg/kg BW alternate day regimen was confirmed in 4 well-controlled studies of naturally acquired bacterial respiratory infections in feedlot age cattle. These studies were conducted under commercial conditions at 4 locations in North America. Bacterial pathogens isolated in the clinical field trial are provided in the Microbiology section.

The effectiveness of ADVOCIN for the control of BRD in cattle at high risk of developing BRD associated with Mannheimia haemolytica and Pasteurella multocida was demonstrated in a multi-site study conducted in North America. The study enrolled a total of 1,480 commercial, crossbred-beef, Holstein and Holstein-cross steer calves at high risk of developing BRD associated with M. haemolytica and P. multocida.

At enrollment, calves were randomly administered a one-time subcutaneous injection of either ADVOCIN at a dosage rate of 8 mg/kg of body weight or an equivalent volume of sterile saline. Cattle were observed daily for clinical signs of BRD and were evaluated for clinical success on Day 10 post-treatment. The treatment success rate of ADVOCIN-treated calves (86.0%) was statistically significantly (p=0.0068) greater than that of saline-treated calves (76.3%) (based on back-transformed least squares means). No adverse events associated with ADVOCIN administration were reported in the study.

ANIMAL SAFETY

Safety studies were conducted in feeder calves using single doses of 10, 20, or 30 mg/kg for 6 consecutive days and 18, 24, or 60 mg/kg for 3 consecutive days. No clinical signs of toxicity were observed at doses of 10 and 20 mg/kg when administered for 6 days, nor at doses of 18 and 24 mg/kg when administered for 3 days. Articular cartilage lesions, consistent with fluoroquinolone chondropathy, were observed after examination of joints from animals as follows: one of 5 animals administered 18 mg/kg for 3 days; one of 6 animals administered 20 mg/kg or 6 days; 5 of 6 animals administered 0 mg/kg for 6 days; and in all 4 animals administered 60 mg/kg for 3 days. Clinical signs of inappetence, transient lameness (2/6), ataxia (2/6), tremors (2/6), nystagmus (1/6), exophthalmos (1/6), and recumbency (2/6) were observed when a dose of 30 mg/kg was administered for 6 consecutive days. Recumbency and depression were seen in one out of 4 animals administered 60 mg/kg for 3 days. Swelling at the injection site was noted at each dose level.

Safety was also evaluated in 21-day-old calves. In one group, these immature animals were given injections of 6 mg/kg on study days 0, 2, 3, 5, 6, and 8. A second group of animals received injections of 18 mg/kg for a total of 2 injections 48 hours apart. The only treatment-related sign was erythema of the nasal pad in 3 of 6 calves that received 18 mg/kg. One calf in the 6 mg/kg group had pretreatment scleral erythema, and developed nasal erythema after treatment that may or may not have been treatment-related. No changes in clinical pathology parameters were observed. No articular cartilage lesions were observed in the joints at any dosage.

An injection site study conducted in feeder calves demonstrated that the product can induce a transient local reaction in the subcutaneous tissue and underlying tissue.

TOXICOLOGY

Ninety-day oral toxicity studies in dogs and rats established a no observable effect level (NOEL) of 2.5 mg/ kg bw/day and 2.4 mg/kg bw/day, respectively. Higher doses in juvenile dogs produced arthropathy, a typical quinolone-associated side effect. In chronic rodent bioassays, no evidence of carcinogenicity was associated with long-term danofloxacin administration in rats and mice. No teratogenic effects were observed in rodents at doses up to 50 mg/kg bw/day (mice) or 100 mg/kg bw/ day (rats) or in rabbits at the highest dose tested of 15 mg/kg bw/day. A three-generation rat reproductive toxicity study established a NOEL of 6.25 mg/kg bw/day. Microbial safety analyses indicate that danofloxacin residues present in edible tissues of treated animals under the current use conditions would most likely not cause adverse effects on the human intestinal microflora of the consumer.

STORAGE INFORMATION

Store at or below 30°C (86°F). Use this product within 28 days of the first puncture and puncture a maximum of 7 times. If more than 7 punctures are anticipated, the use of automatic injection equipment or a repeater syringe is recommended. When using a draw-off spike or needle with bore diameter larger than 16 gauge, discard any product remaining in the vial immediately after use. Protect from light. Protect from freezing. The color is yellow to amber and does not affect potency.

HOW SUPPLIED

ADVOCIN (180 mg danofloxacin/mL) is supplied in 100- and 250-mL, amber-glass, sterile, multi-dose vials.

Approved by FDA under NADA # 141-207

zoetis

Distributed by:

Zoetis Inc.Kalamazoo, MI 49007

Use Only as Directed

CONTACT INFORMATION

To report suspected adverse effects and/or obtain a copy of the SDS or for technical assistance, call Zoetis Inc. at
1-888-963-8471.
For additional information about adverse drug experience reporting for animal drugs, contact FDA at 1-888-FDA-VETS
or online at www.fda.gov/reportanimalae.

TAKE TIME |  | OBSERVE LABEL DIRECTIONS

Revised: October 2020

40032874

40032877